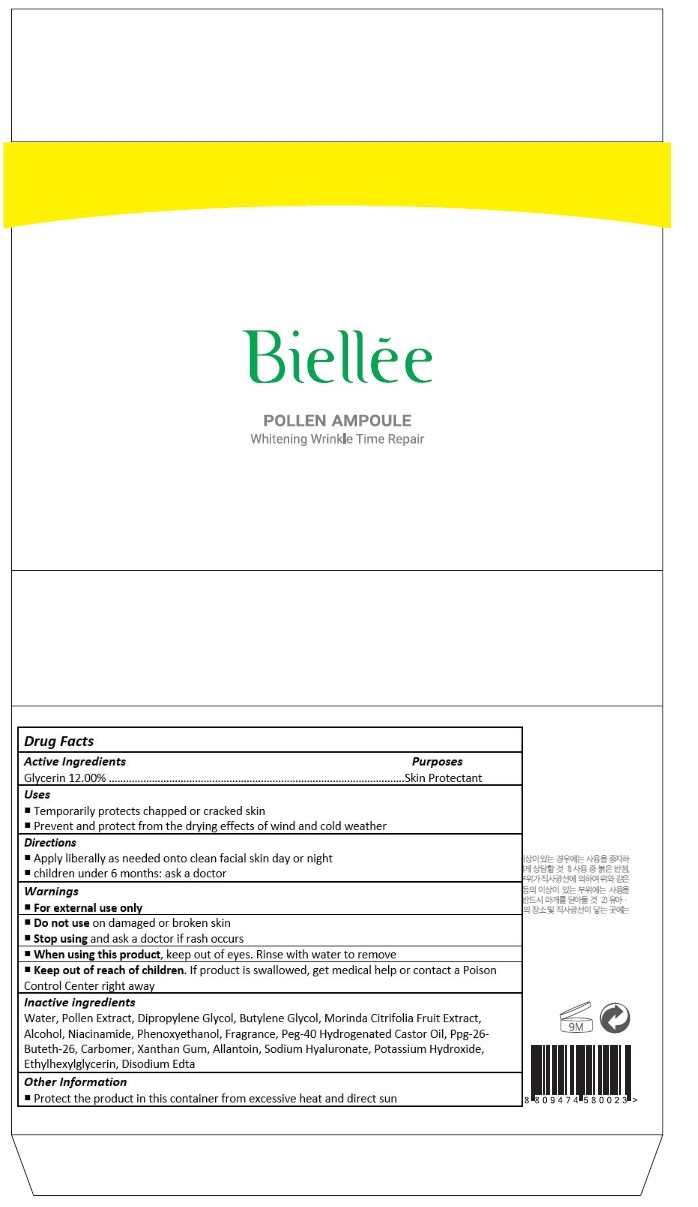 DRUG LABEL: Biellee Pollen Whitening Wrinkle Time Repair Ampoule
NDC: 70784-001 | Form: CREAM
Manufacturer: NSB CO., LTD.
Category: otc | Type: HUMAN OTC DRUG LABEL
Date: 20160621

ACTIVE INGREDIENTS: GLYCERIN 1.2 mg/10 mL
INACTIVE INGREDIENTS: WATER; BEE POLLEN; DIPROPYLENE GLYCOL; BUTYLENE GLYCOL; NONI FRUIT; ALCOHOL; NIACINAMIDE; PHENOXYETHANOL; POLYOXYL 40 HYDROGENATED CASTOR OIL; PPG-26-BUTETH-26; CARBOXYPOLYMETHYLENE; XANTHAN GUM; ALLANTOIN; HYALURONATE SODIUM; POTASSIUM HYDROXIDE; ETHYLHEXYLGLYCERIN; EDETATE DISODIUM

Drug Facts

ACTIVE INGREDIENT

GLYCERIN 12.00%

PURPOSE

Skin Protectant

INDICATIONS AND USAGE

Temporarily protects chapped or cracked skin
Prevent and protect from the drying effects of wind and cold weather

DOSAGE AND ADMINISTRATION

Apply liberally as needed onto clean facial skin day or night
Children under 6 months: ask a doctor

WARNINGS

For external use only

Do not use on damaged or broken skin

When using this product, keep out of eyes. Rinse with water to remove.

Stop using and ask a doctor if rash occurs.

KEEP OUT OF REACH OF CHILDREN

Keep out of reach of the children. If product is swallowed, get medical help or contact a poison control center right away.

INACTIVE INGREDIENT

WATER
POLLEN EXTRACT
DIPROPYLENE GLYCOL
BUTYLENE GLYCOL
MORINDA CITRIFOLIA FRUIT EXTRACT
ALCOHOL
NIACINAMIDE
PHENOXYETHANOL
FRAGRANCE
PEG-40 HYDROGENATED CASTOR OIL
PPG-26-BUTETH-26
CARBOMER
XANTHAN GUM
ALLANTOIN
SODIUM HYALURONATE
POTASSIUM HYDROXIDE
ETHYLHEXYLGLYCERIN
DISODIUM EDTA